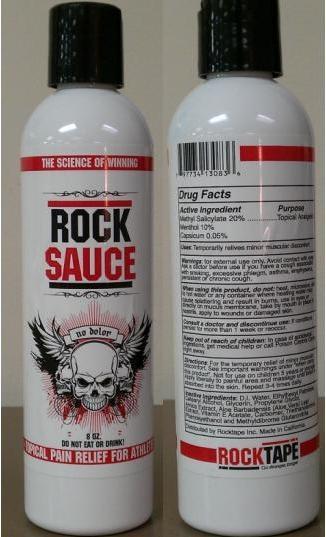 DRUG LABEL: ROCK SAUCE
                
NDC: 59663-100 | Form: LOTION
Manufacturer: Shine & Pretty (USA), Corp.
Category: otc | Type: HUMAN OTC DRUG LABEL
Date: 20120602

ACTIVE INGREDIENTS: METHYL SALICYLATE 20 mL/100 mL; MENTHOL 10 mL/100 mL; CAPSICUM 0.05 mL/100 mL
INACTIVE INGREDIENTS: WATER; ETHYLHEXYL PALMITATE; CETOSTEARYL ALCOHOL; GLYCERIN; PROPYLENE GLYCOL; ARNICA MONTANA; ALOE VERA LEAF; ALPHA-TOCOPHEROL ACETATE; CARBOMER 934; TROLAMINE; PHENOXYETHANOL; METHYLDIBROMO GLUTARONITRILE

PURPOSE

Uses: Temporarily relives minor muscular discomfort

When using this product, do not: heat, microwave, add to hot water or any container where heating water may cause splatterring and result in burns, use in eyes or directly on mucus membrane, take by month or place in nostrils, apply to wounds or damaged skin.

WARNINGS

Warnings: For external use only. Avoid contact with eyes. Ask a doctor before use if you have a cough associated with smoking, excessive phlegm, asthma, emphysema, persistent or chronic cough.

DOSAGE AND ADMINISTRATION

Directions: For the temporary relief of minor muscular discomfort. See important warnings under "When using this product". Not for use on children 5 years or younger. Apply liberally to painful area and massage until lotion is absorbed into the skin. Repeat 3-4 times daily.

INACTIVE INGREDIENT

Inactive Ingredients: D. I. Water, Ethylhexyl Palmitate, Cetearyl Alcohol, Glycerin, Propylene Glycol, Arnica Extract, Aloe Barbadensis (Aloe Vera) Leaf Extract, Vitamin E Acetate, Carbomer, Triethanolamine, Phenoxyethanol and Methyldibrome Glutarontrile

KEEP OUT OF REACH OF CHILDREN

Keep out of the reach of children: In case of accidental ingestions, get medical help or call Poison Control Center right away.

Active Ingredient

Methyl Salicylate 20%

Menthol 10%

Capsicum 0.05%

PATIENT COUNSELING INFORMATION

Consult a doctor and discontinue use: If conditions persist for more than 1 week or reoccur.

PACKAGE LABEL

MM1